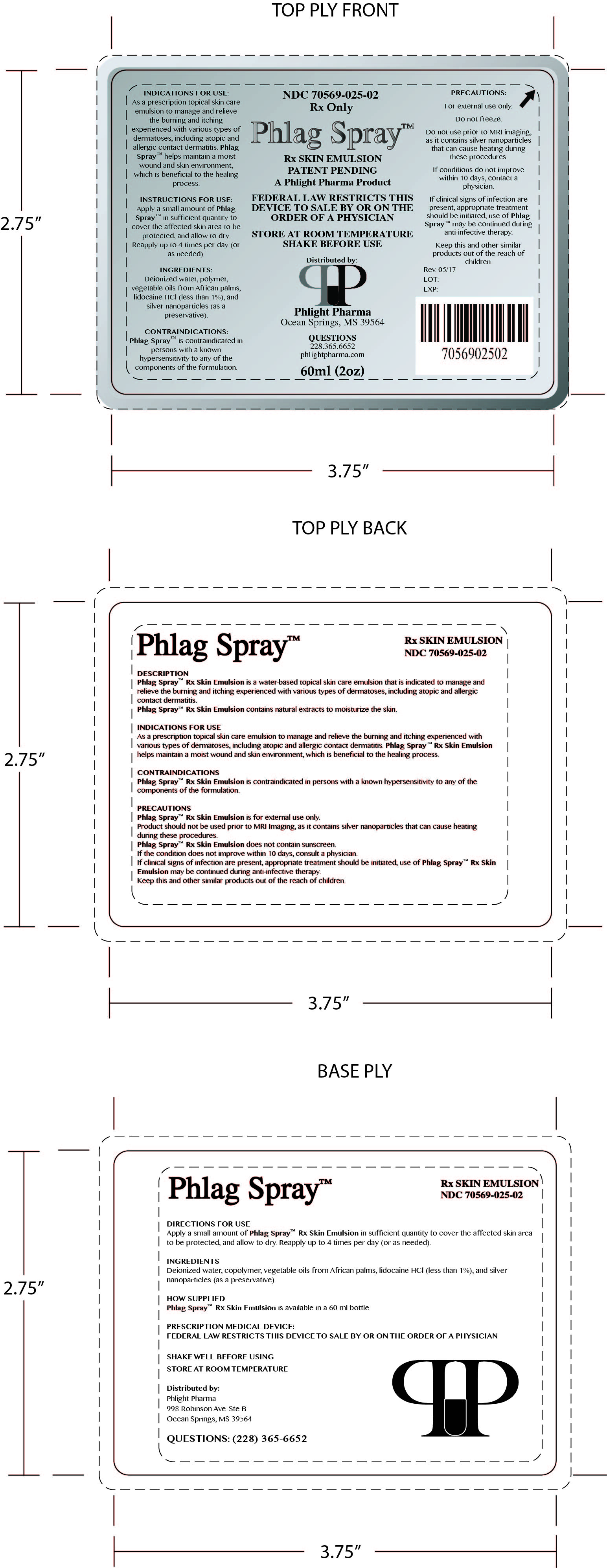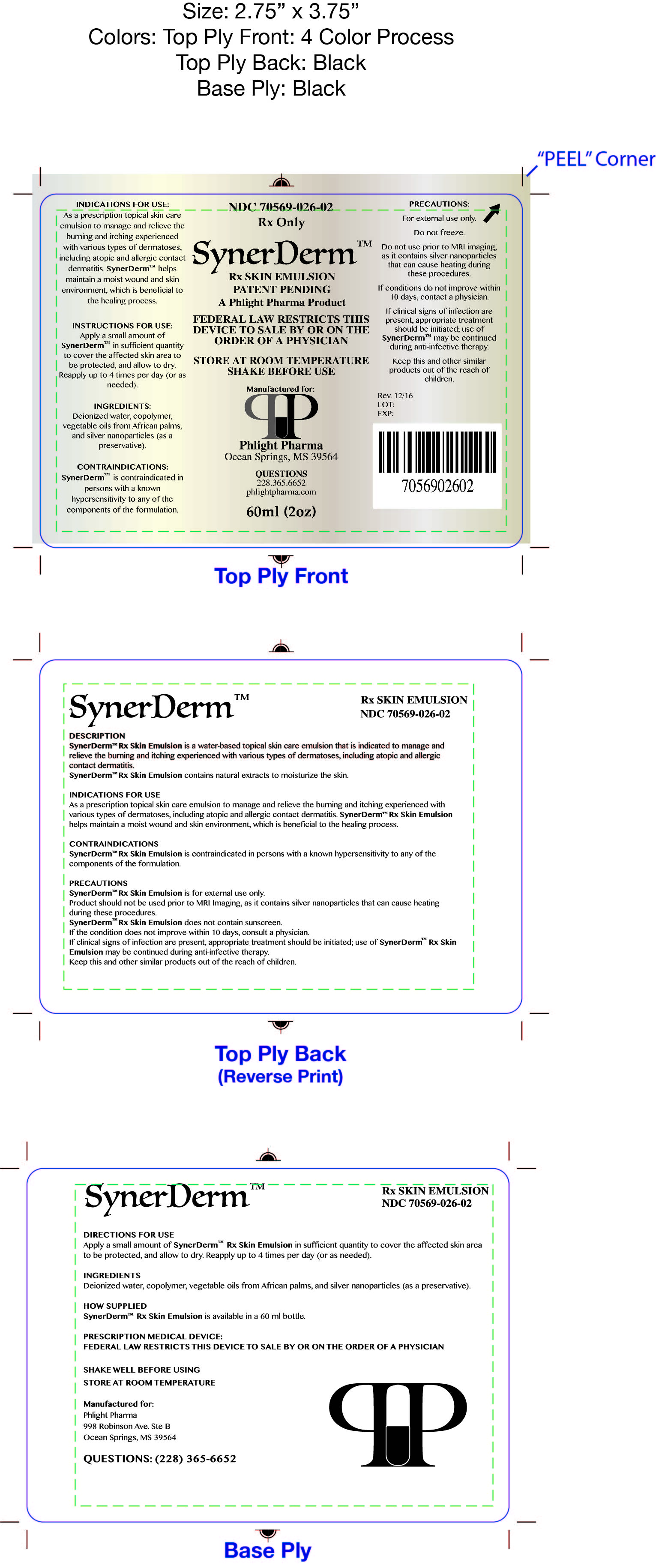 DRUG LABEL: Phlag Spray Rx Skin Emulsion
NDC: 70569-025
Manufacturer: Phlight Pharma
Category: other | Type: PRESCRIPTION MEDICAL DEVICE LABEL
Date: 20170523

Phlag Spray Rx Skin Emulsion and SynerDerm Rx Skin Emulsion

DESCRIPTION

Phlag Spray Rx Skin Emulsion & SynerDerm Rx Skin Emulsion are water-based topical skin care emulsions that are indicated to manage and relieve the burning and itching experienced with various types of dermatoses, including atopic and allergic contact dermatitis. Phlag Spray Rx Skin Emulsion & SynerDerm Rx Skin Emulsion contain natural extracts to moisturize the skin.

INDICATIONS & USAGE

Phlag Spray Rx Skin Emulsion & SynerDerm Rx Skin Emulsion are indicated as a prescription topical skin care emulsion to manage and relieve the burning and itching experienced with various types of dermatoses, including atopic and allergic contact dermatitis. Phlag Spray Rx Skin Emulsion helps maintain a moist wound and skin environment, which is beneficial to the healing process.

CONTRAINDICATIONS

Phlag Spray Rx Skin Emulsion & SynerDerm Rx Skin Emulsion are contraindicated in persons with a known hypersensitivity to any of the components of the formulation.

PRECAUTIONS

Phlag Spray Rx Skin Emulsion & SynerDerm Rx Skin Emulsion is for external use only.

Product should not be used prior to MRI Imaging, as it contains silver nanoparticles that can cause heating during these procedures.

Phlag Spray Rx Skin Emulsion & SynerDerm Rx Skin Emulsion does not contain sunscreen. If the condition does not improve within 10 days, consult a physician. If clinical signs of infection are present, appropriate treatment should be initiated; use of Phlag Spray Rx Skin Emulsion & SynerDerm Rx Skin Emulsion may be continued during anti-infective therapy.

Keep this and other similar products out of the reach of children.

INSTRUCTIONS FOR USE

Shake well before use. Apply a small amount of product in sufficient quantity to cover the affected skin area to be protected, and allow to dry. Reapply up to 4 times per day (or as needed).

INGREDIENTS

Phlag Spray Rx Skin Emulsion contains deionized water, copolymer, vegetable oils from African palms, lidocaine HCl (less than 1%), and silver nanoparticles (as a preservative).

SynerDerm Rx Skin Emulsion contains deionized water, copolymer, vegetable oils from African palms, and silver nanoparticles (as a preservative).

HOW SUPPLIED

Phlag Spray Rx Skin Emulsion is available in 60mL bottles, NDC 70569-025-02.

SynerDerm Rx Skin Emulsion is available in 60mL bottles, NDC 70569-026-02.

Shake well before using.

Store at room temperature. Do not freeze.

Phlight Pharma

998 Robinson Ave. Ste B

Ocean Springs, MS 39564